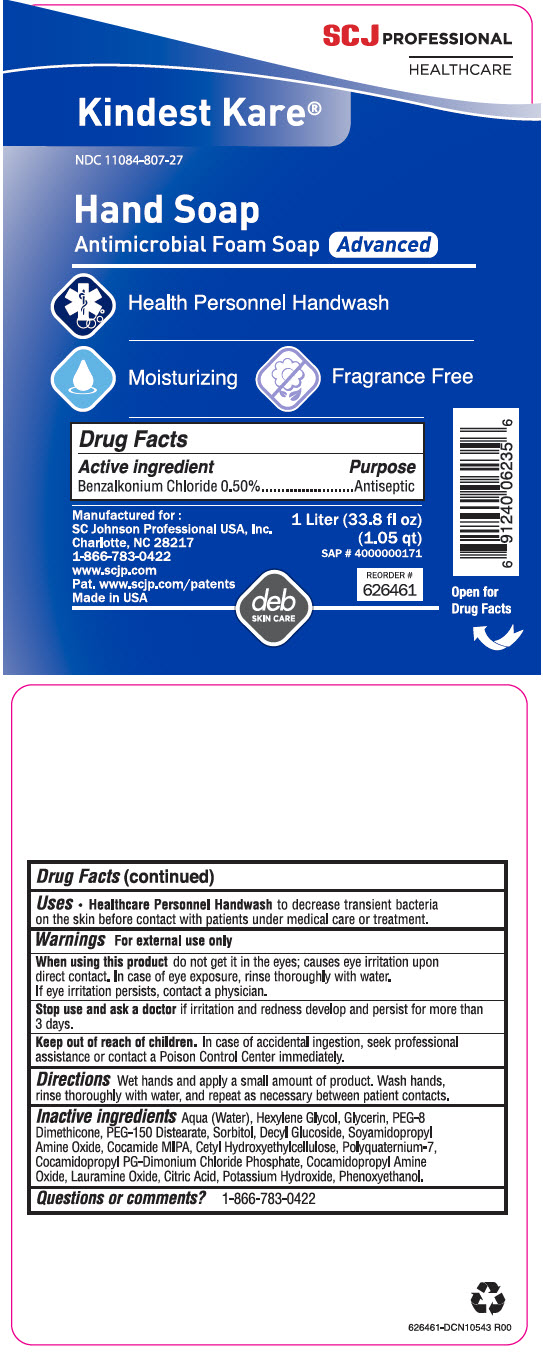 DRUG LABEL: Kindest Kare Advanced Antimicrobial Foam Handwash
NDC: 11084-807 | Form: LIQUID
Manufacturer: SC Johnson Professional USA, Inc.
Category: otc | Type: HUMAN OTC DRUG LABEL
Date: 20250620

ACTIVE INGREDIENTS: BENZALKONIUM CHLORIDE 0.5 mg/100 mL
INACTIVE INGREDIENTS: WATER; HEXYLENE GLYCOL; GLYCERIN; PEG-8 DIMETHICONE (600 CST); PEG-150 DISTEARATE; SORBITOL; DECYL GLUCOSIDE; COCO MONOISOPROPANOLAMIDE; CETYL HYDROXYETHYLCELLULOSE (350000 MW); POLYQUATERNIUM-7 (70/30 ACRYLAMIDE/DADMAC; 1600000 MW); COCAMIDOPROPYL PROPYLENE GLYCOL-DIMONIUM CHLORIDE PHOSPHATE; COCAMIDOPROPYLAMINE OXIDE; LAURAMINE OXIDE; CITRIC ACID MONOHYDRATE; POTASSIUM HYDROXIDE; PHENOXYETHANOL

Kindest Kare® Advanced Antimicrobial Foam Handwash

Drug Facts

Active Ingredient

Benzalkonium Chloride 0.50%

Purpose

Antiseptic

Uses

- Healthcare Personnel Handwash to decrease transient bacteria on the skin before contact with patients under medical care or treatments.

Warnings

For external use only

When using this product do not get it in the eyes; causes eye irritation upon direct contact. In case of eye exposure, rinse thoroughly with water. If eye irritation persists, contact a physician.

Stop use and ask a doctor if irritation and redness develop and persist for more than 3 days.

Keep out of reach of children. In case of accidental ingestion, seek professional assistance or contact a Poison Control Center immediately.

Directions

Wet hands and apply a small amount of product. Wash hands, rinse thoroughly with water, and repeat as necessary between patient contacts.

Inactive ingredients

Aqua (Water), Hexylene Glycol, Glycerin, PEG-8 Dimethicone, PEG-150 Distearate, Sorbitol, Decyl Glucoside, Soyamidopropyl Amine Oxide, Cocamide MIPA, Cetyl Hydroxyethylcellulose, Polyquaternium-7, Cocamidopropyl PG-Dimonium Chloride Phosphate, Cocamidopropyl Amine Oxide, Lauramine Oxide, Citric Acid, Potassium Hydroxide, Phenoxyethanol.

Questions or comments?

1-866-783-0422

PRINCIPAL DISPLAY PANEL - 1 Liter Bottle Label

SCJ PROFESSIONAL
HEALTHCARE

Kindest Kare®

NDC 11084-807-27

Hand Soap
Antimicrobial Foam Soap Advanced

Health Personnel Handwash

Moisturizing
Fragrance Free

Manufactured for :
SC Johnson Professional USA, Inc.
Charlotte, NC 28217
1-866-783-0422
www.scjp.com
Pat. www.scjp.com/patents
Made in USA

1 Liter (33.8 fl oz)
(1.05 qt)

SAP # 4000000171

REORDER #
626461

deb
SKIN CARE

Open for
Drug Facts